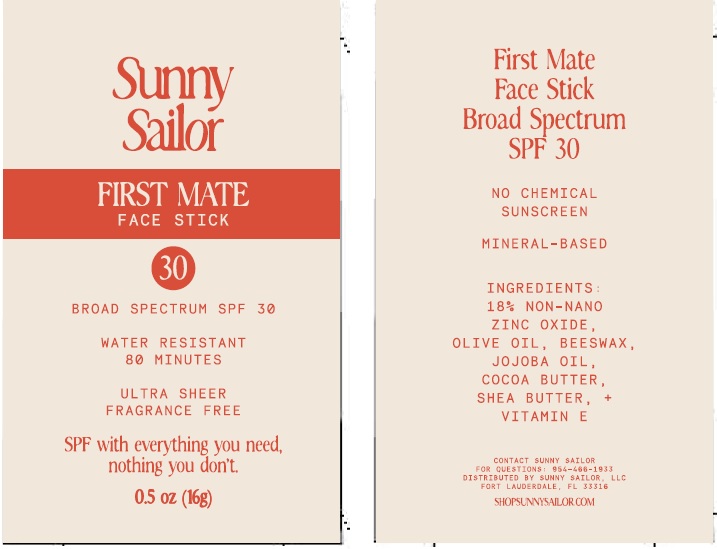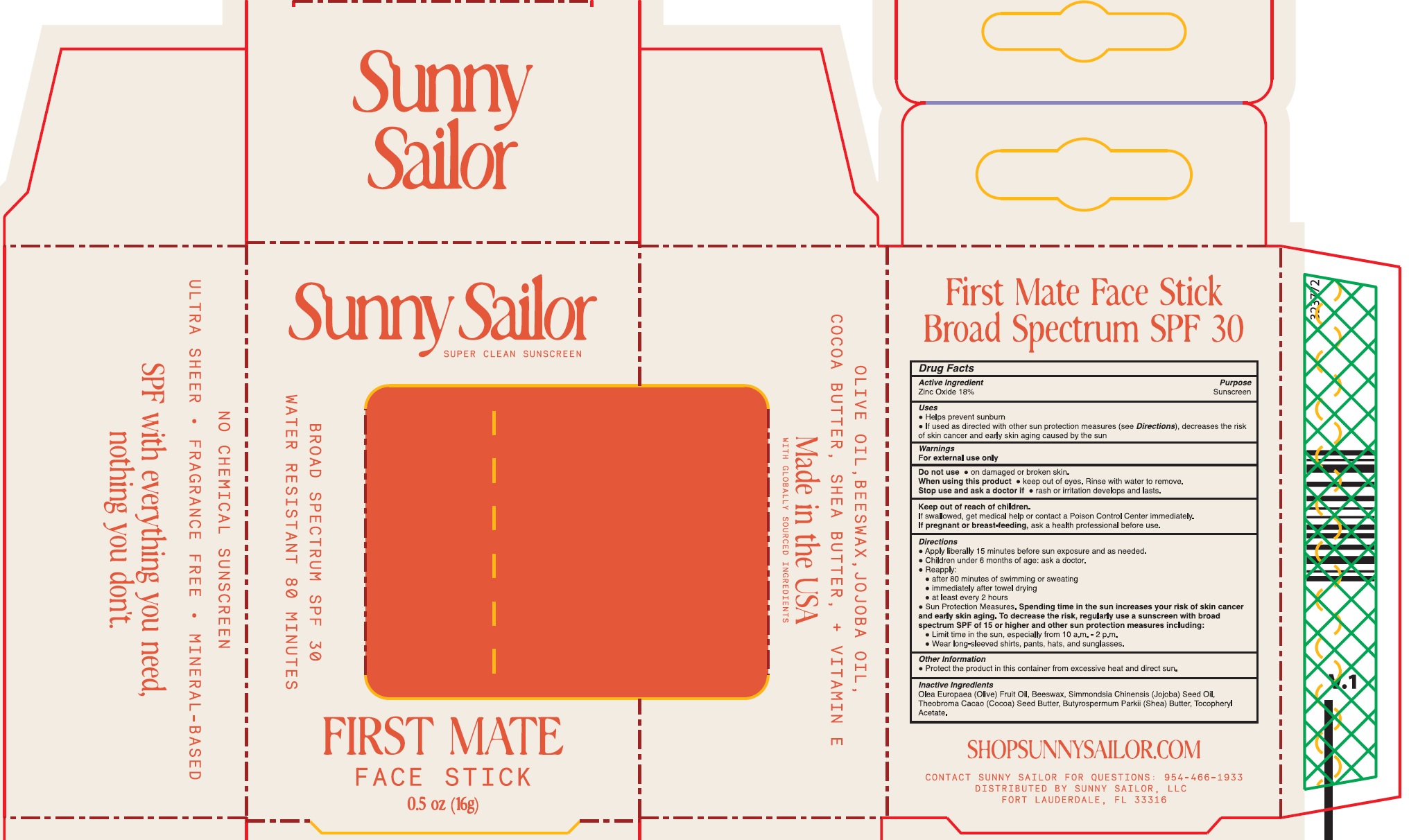 DRUG LABEL: Sunny Sailor First Mate Face Stick SPF 30
NDC: 85135-896 | Form: STICK
Manufacturer: SUNNY SAILOR LLC
Category: otc | Type: HUMAN OTC DRUG LABEL
Date: 20251013

ACTIVE INGREDIENTS: ZINC OXIDE 180 mg/1 g
INACTIVE INGREDIENTS: OLIVE OIL; YELLOW WAX; JOJOBA OIL; COCOA BUTTER; SHEA BUTTER; .ALPHA.-TOCOPHEROL ACETATE

Sunny Sailor First Mate Face Stick SPF 30

Active Ingredient

Zinc Oxide 18%

Purpose

Sunscreen

Uses

- Helps prevent sunburn
- If used as directed with other sun protection measures (see Directions), decreases the risk of skin cancer and early skin aging caused by the sun

Warnings

For external use only

Do not use

- on damaged or broken skin.

When using this product

- keep out of eyes. Rinse with water to remove.

Stop use and ask a doctor if

- rash or irritation develops and lasts.

Keep out of reach of children.

If swallowed, get medical help or contact a Poison Control Center immediately.

If pregnant or breast-feeding,

ask a health professional before use.

Directions

- Apply liberally 15 minutes before sun exposure and as needed.
- Children under 6 months of age: ask a doctor.
- Reapply:
- after 80 minutes of swimming or sweating.
- immediately after towel drying.
- at least every 2 hours
- Sun Protection Measures. Spending time in the sun increases your risk of skin cancer and early skin aging. To decrease the risk, regularly use a sunscreen with broad spectrum SPF of 15 or higher and other sun protection measures including:
- Limit time in the sun, especially from 10 a.m - 2 p.m.
- Wear long-sleeved shirts, pants, hats, and sunglasses.

Other Information

- Protect the product in this container from excessive heat and direct sun.

INACTIVE INGREDIENTS

Olea Europaea (Olive) Fruit Oil, Beeswax, Simmondsia Chinensis (Jojoba) Seed Oil, Theobroma Cacao (Cocoa) Seed Butter, Butyrospermum Parkii (Shea) Butter, Tocopheryl Acetate.